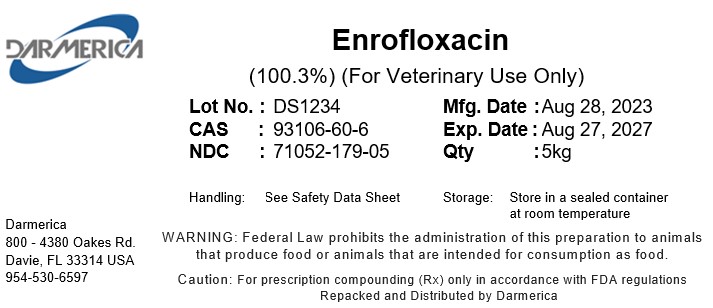 DRUG LABEL: Enrofloxacin Base
NDC: 71052-179 | Form: POWDER
Manufacturer: DARMERICA, LLC
Category: other | Type: BULK INGREDIENT - ANIMAL DRUG
Date: 20241220

ACTIVE INGREDIENTS: ENROFLOXACIN 1 kg/1 kg

Enrofloxacin